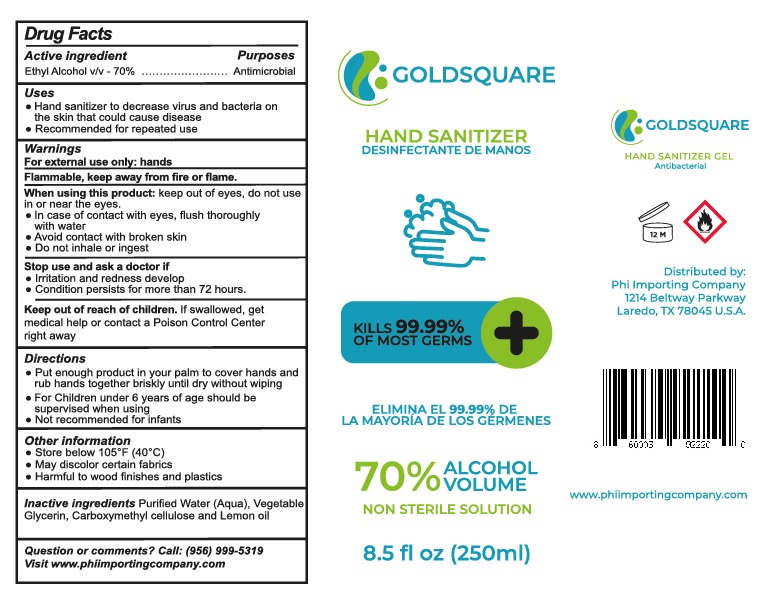 DRUG LABEL: HAND SANITIZER
NDC: 77210-0013 | Form: GEL
Manufacturer: EXPORTADORA IN & OUT SR DE CV
Category: otc | Type: HUMAN OTC DRUG LABEL
Date: 20200626

ACTIVE INGREDIENTS: ALCOHOL 70 mL/100 mL
INACTIVE INGREDIENTS: CARBOXYMETHYLCELLULOSE; GLYCERIN; LEMON OIL; WATER

Active ingredient

ethyl alcohol v/v - 70%

Purposes

Antimicrobial

Uses

hand sanitizer to decrease bacteria on the skin that could cause disease

recommended for repetead use

Warnings

for external use only: hands

flammable, keep away from fire and flame

When using this product

keep out of eyes, do not use in or near the eyes

in case of contact with eyes, flush thorougly with water

avoid contact with broken skin

When using this product

keep out of eyes, do not use in or near the eyes

in case of contact with eyes, flush thorougly with water

avoid contact with broken skin

Stop use and ask a doctor if

irritation and redness develo

condition persists for more than 72 hours

Keep out of reach of children

if swallowed, get medical help or contact a posion control center right away

Directions

put enough product in your palm to cover hands and rub hands together briskly until dry without wiping

for children under 6 years of age should be supervised when using

not recommended for infants

Other information

store below 105 F (40C)

may discolor certain fabrics

harmful to wood finishes and plastics

Inactive ingredients

Purified water (aqua), vegetable glycerin, carboxymethyl cellulose and lemon oil

Principal Display

Hand sanitizer

desinfectante de manos

kills 99.99% of most germs

elimina el 99.9% de la mayria de los germenes

70% alcohol volume

non sterile solution

antibacterial